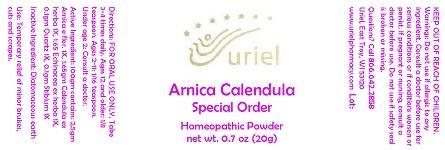 DRUG LABEL: Arnica Calendula Special Order
NDC: 48951-1248 | Form: POWDER
Manufacturer: Uriel Pharmacy Inc.
Category: homeopathic | Type: HUMAN OTC DRUG LABEL
Date: 20140929

ACTIVE INGREDIENTS: ARNICA MONTANA FLOWER 1 [hp_X]/1 g; CALENDULA OFFICINALIS FLOWERING TOP 1 [hp_X]/1 g; ECHINACEA ANGUSTIFOLIA 1 [hp_X]/1 g; COLLOIDAL SILICON DIOXIDE 1 [hp_X]/1 g; ANTIMONY 1 [hp_X]/1 g
INACTIVE INGREDIENTS: DIATOMACEOUS EARTH

Arnica Calendula Special Order

INDICATIONS AND USAGE

Directions: FOR ORAL USE ONLY.

DOSAGE AND ADMINISTRATION

Take 3-4 times daily. Ages 12 and older: 1/8 teaspoon. Ages 2-11: 1/16 teaspoon. Under age 2: Consult a doctor.

Active Ingredient: 100gm contains: 2.5gm Arnica e flor. 1X, 1.65gm Calendula ex herba 1X, 1.65 Echinacea ex herba 1X, 0.1gm Quartz 1X, 0.1gm Stibium 1X

Inactive Ingredient: Diatomaceous earth

PURPOSE

Use: Temporary relief of minor bruises, cuts and scrapes.

KEEP OUT OF REACH OF CHILDREN.

WARNINGS

Warnings: Do not use if allergic to any ingredient. Consult a doctor before use for serious conditions or if conditions worsen or persist. If pregnant or nursing, consult a doctor before use. Do not use if safety seal is broken or missing.

QUESTIONS

Questions? Call 866.642.2858 Uriel, East Troy, WI 53120 www.urielpharmacy.com